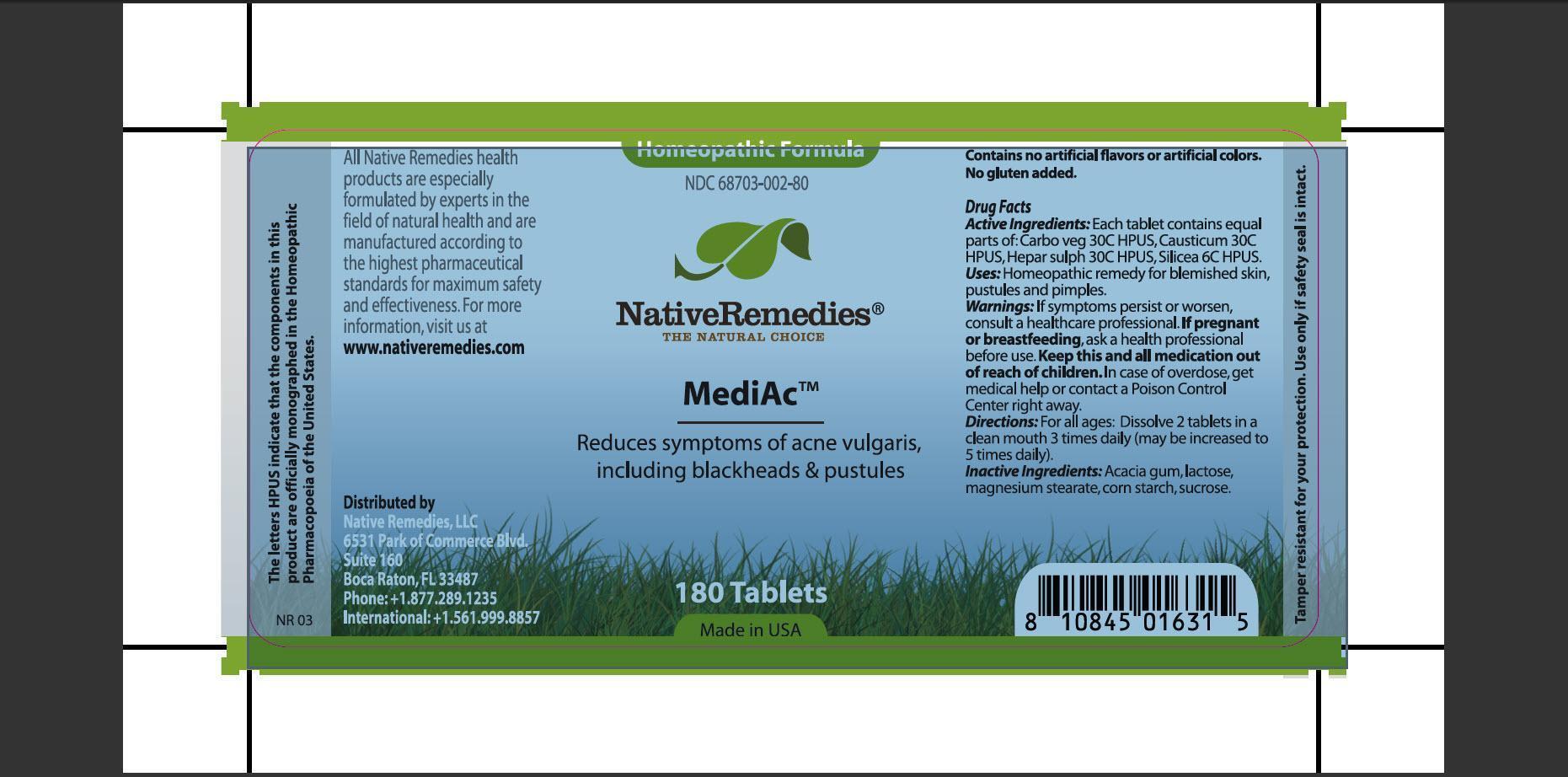 DRUG LABEL: MediAc
NDC: 68703-002 | Form: TABLET
Manufacturer: Native Remedies LLC
Category: homeopathic | Type: HUMAN OTC DRUG LABEL
Date: 20130115

ACTIVE INGREDIENTS: ACTIVATED CHARCOAL 30 [hp_C]/1 1; CAUSTICUM 30 [hp_C]/1 1; CALCIUM SULFIDE 30 [hp_C]/1 1; SILICON DIOXIDE 6 [hp_C]/1 1
INACTIVE INGREDIENTS: ACACIA; LACTOSE; MAGNESIUM STEARATE; STARCH, CORN; SUCROSE

MediAc

PURPOSE

Reduces sysmptoms of acne vulgaris, including blackheads and pustules.

ACTIVE INGREDIENT

Active Ingredients: Each tablet contains equal parts of: Carbo veg 30C HPUS, Causticum 30C HPUS, Hepar sulph 30C HPUS, Silicea 6C HPUS.

INDICATIONS AND USAGE

Uses: Homeopathic remedy for blemished skin, postules and pimples.

WARNINGS

Warning: If symptoms persist or worsen, consult a healthcare professional.

PREGNANCY OR BREAST FEEDING

If pregnant or breastfeeding, ask health professional before use.

KEEP OUT OF REACH OF CHILDREN

Keep this and all medication out of reach of children.

OVERDOSAGE

In case of overdose, get medical help or contact a Poison Control Center right away.

DOSAGE AND ADMINISTRATION

Directions: For all ages: Dissolve 2 tablets in a clean mouth 3 times daily (may be increased to 5 times daily).

INACTIVE INGREDIENT

Inactive Ingredients: Acacia gum, lactose, magnesium stearate, cor starch, sucrose.

PATIENT COUNSELING INFORMATION

The letters HPUS indicate that the components in this product are officially monographed in the Homeopathic Pharmacopoeia of the United States.

All Native Remedies health products are especially formulated by experts in the field of natural health and are manufactures according to the highest pharmaceutical standards for maximum safety and effectiveness. For more information, visit us at www.nativeremedies.com

Distributed by
Native Remedies, LLC
6531 Park of Commerce Blvd.
Suite 160
Boca Raton, FL 33487
Phone:+1.877.286.1235
International:+1.561.999.8857

Contains no artificial flavors or artificial colors No gluten added.

STORAGE AND HANDLING

Tamper resistant for your protection. Use only if safety seal is intact.